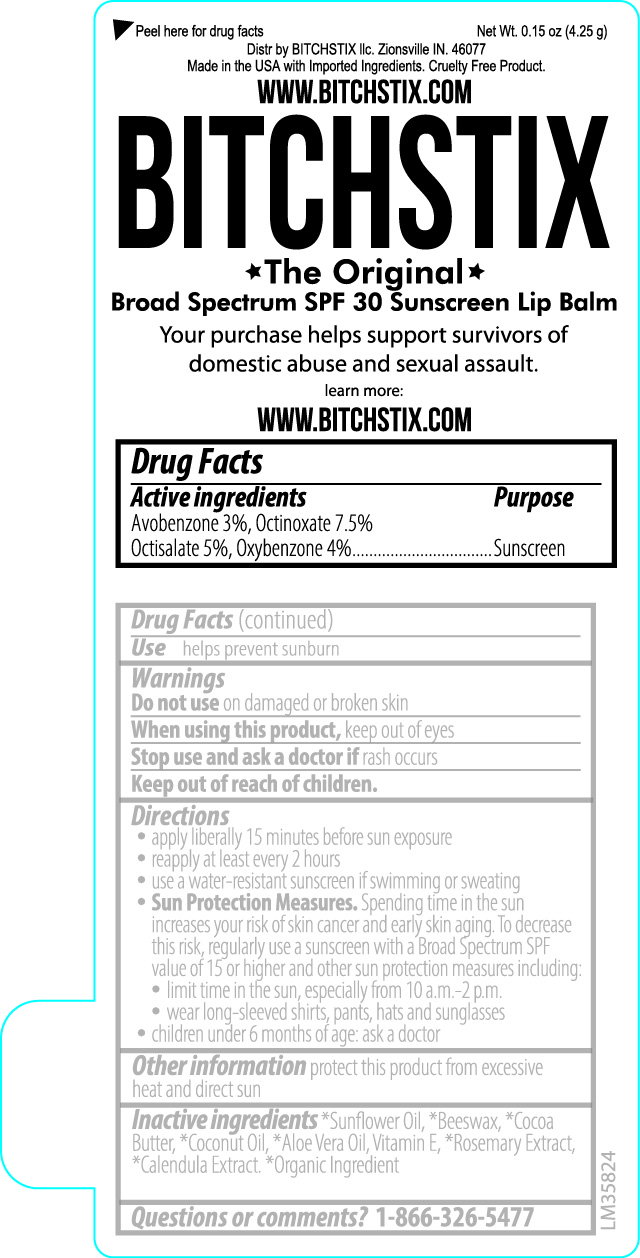 DRUG LABEL: Bitchstix The Original SPF 30 Sunscreen Lip Balm
NDC: 84438-901 | Form: STICK
Manufacturer: Bitchistix, LLC
Category: otc | Type: HUMAN OTC DRUG LABEL
Date: 20240717

ACTIVE INGREDIENTS: OCTINOXATE 7.5 g/100 g; OXYBENZONE 4 g/100 g; AVOBENZONE 3 g/100 g; OCTISALATE 5 g/100 g
INACTIVE INGREDIENTS: COCONUT OIL; ROSEMARY OIL; ALOE VERA LEAF; CALENDULA OFFICINALIS FLOWER; YELLOW WAX; SUNFLOWER OIL; COCOA BUTTER; TOCOPHEROL

99901 Bitchstix The Original (Unflavored) SPF 30 Lip Balm

Drug Facts

Active ingredients

Avobenzone 3%, Octinoxate 7.5%

Octisalate 5%, Oxybenzone 4%

Purpose

Sunscreen

Use

helps prevent sunburn

Warnings

Do not useon damaged or broken skin

When using this productkeep out of eyes

Stop use and ask a doctor ifrash occurs

Keep out of reach of children.

Directions

- apply liberally 15 minutes before sun exposure
- reapply at least every 2 hours
- use a water-resistant sunscreen if swimming or sweating
- Sun Protection Measures. Spending time in the sun increases your risk of skin cancer and early skin aging. To decrease this risk, regularly use a sunscreen with a Broad Spectrum SPF value of 15 or higher and other sun protection measures including:
- limit time in the sun, especially from 10 a.m. - 2 p.m.
- wear long-sleeved shirts, pants, hats and sunglasses
- children under 6 months of age: ask a doctor

STORAGE AND HANDLING

Other informationprotect this product from excessive heat and direct sun

INACTIVE INGREDIENT

Inactive ingredients*Sunflower Oil, *Beeswax, *Cocoa Butter, *Coconut Oil, , *Aloe Vera Oil, Vitamin E, *Rosmarinus Extract, *Calendula Extract. *Organic Ingredient

Questions or comments?1-866-326-5477

Peel here for drug facts Net Wt. 0.15 oz (4.25 g)

Made in the USA with Imported Ingredients. Cruelty Free Product.

WWW.BITCHSTIX.COM

BITCHSTIX

The Original

Broad Spectrum SPF 30 Sunscreen Lip Balm

Your purchase helps support survivors of domestic abuse and sexual assault.

learn more:

WWW.BITCHSTIX.COM

PACKAGE LABEL

Net Wt.. .15oz (4.25g)